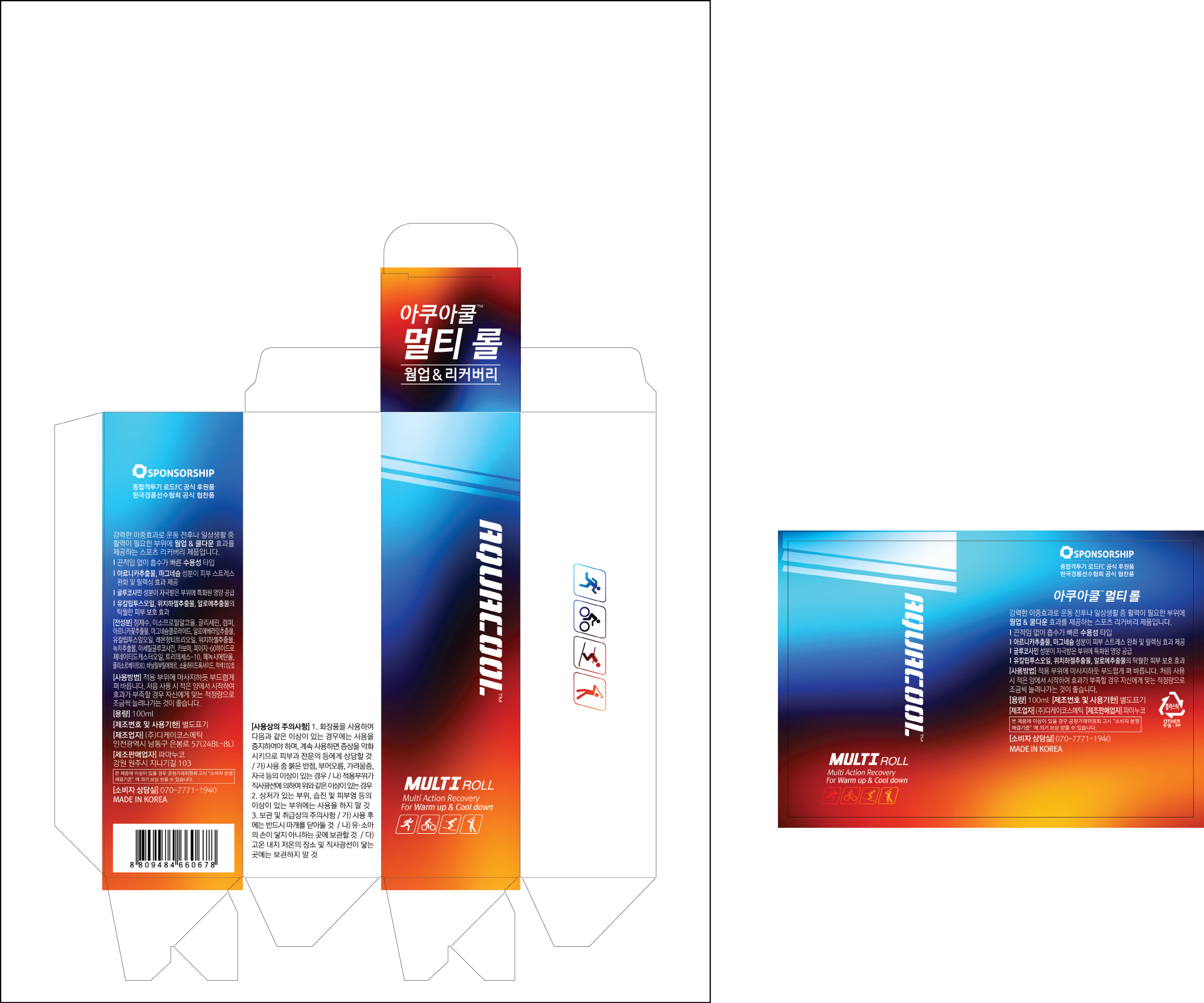 DRUG LABEL: AQUACOOL MULTI 120
NDC: 70759-0011 | Form: GEL
Manufacturer: Pharmanuco
Category: otc | Type: HUMAN OTC DRUG LABEL
Date: 20210309

ACTIVE INGREDIENTS: MENTHOL 3 g/100 mL
INACTIVE INGREDIENTS: EUCALYPTUS GLOBULUS LEAF; CAMPHOR, (-)-; ARNICA MONTANA FLOWER; WITCH HAZEL; ALOE VERA LEAF; N-ACETYLGLUCOSAMINE

Drug Facts

ACTIVE INGREDIENT

MENTHOL

INACTIVE INGREDIENT

Camphor, Carbomer, Eucalyptus Globulus Leaf Oil, Witch Hazel Extract, Arnica Montana Flower Extract, Aloe Barbadensis Leaf Extract, Acetyl Glucosamine, etc.

PURPOSE

External Analgesic: Multi Action Recovery for Warm Up & Cool Down

keep out of reach of the children

INDICATIONS AND USAGE

1. Apply gel on to affected areas.

2. Massage until completely absorbed into skin.

3. Repeat as many as needed.

* It is recommended to control the amount and times of use depending on your symptom.

DOSAGE AND ADMINISTRATION

for external use only

WARNINGS

Avoid contact with eyes. Stop if irritation occurs. Avoid bandaging tightly. Keep out of reach of children. Ask your doctor before use if pregnant or breast feeding